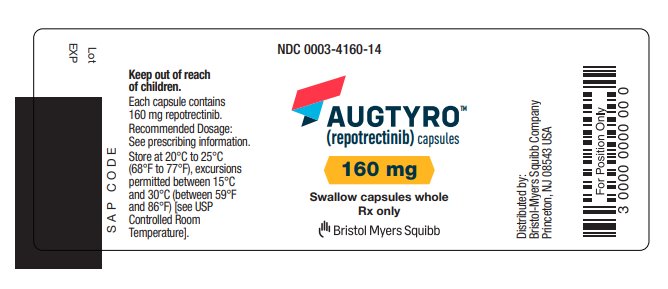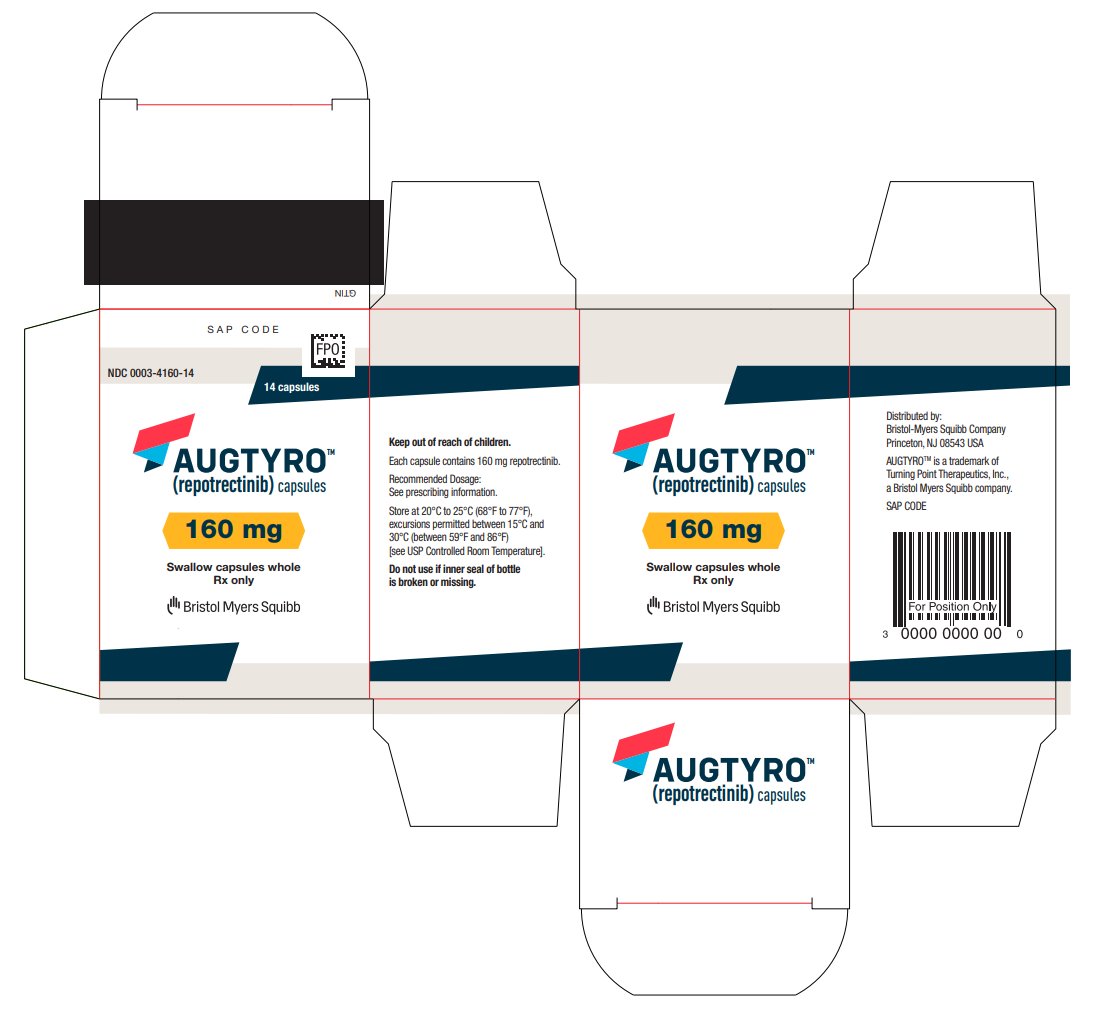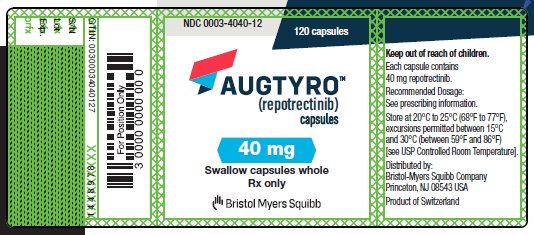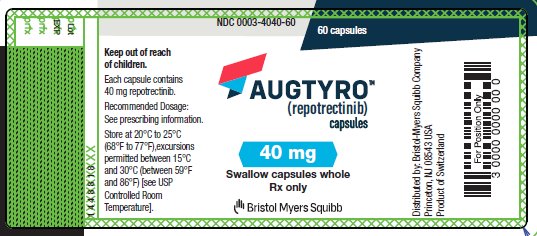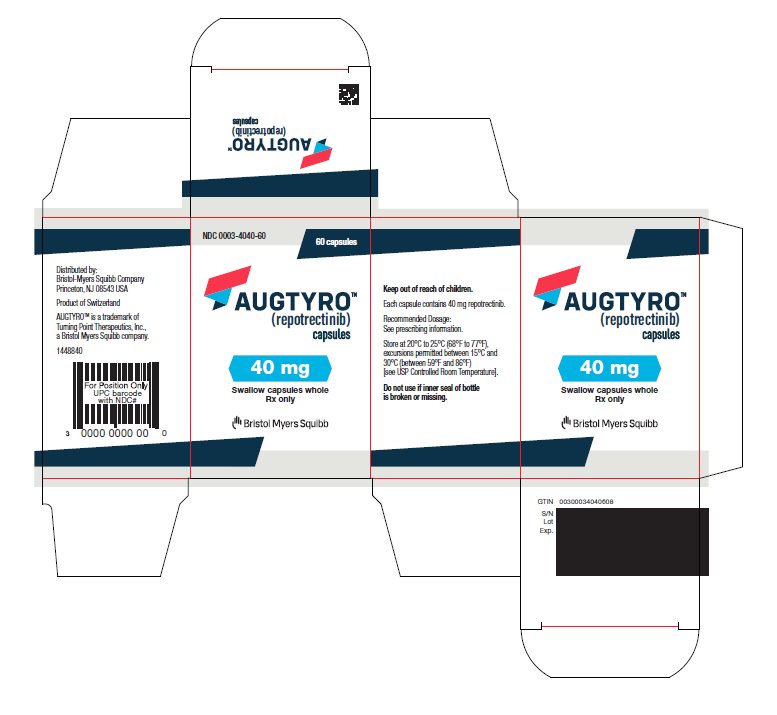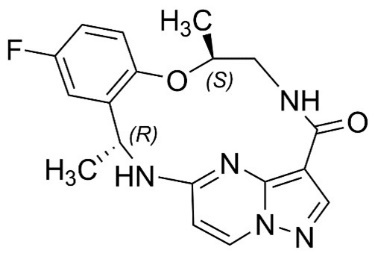 DRUG LABEL: Augtyro
NDC: 0003-4040 | Form: CAPSULE
Manufacturer: E.R. Squibb & Sons, L.L.C.
Category: prescription | Type: HUMAN PRESCRIPTION DRUG LABEL
Date: 20240613

ACTIVE INGREDIENTS: REPOTRECTINIB 40 mg/1 1
INACTIVE INGREDIENTS: MICROCRYSTALLINE CELLULOSE; SODIUM LAURYL SULFATE; CROSCARMELLOSE SODIUM; SILICON DIOXIDE

HIGHLIGHTS OF PRESCRIBING INFORMATION

These highlights do not include all the information needed to use AUGTYRO safely and effectively. See full prescribing information for AUGTYRO.
AUGTYROTM (repotrectinib) capsules, for oral use
Initial U.S. Approval: 2023

RECENT MAJOR CHANGES

Indications and Usage (1.2) | 06/2024
Dosage and Administration (2.1) | 06/2024
Warnings and Precautions (5.6) | 06/2024

1 INDICATIONS AND USAGE

AUGTYRO is a kinase inhibitor indicated for the treatment of

- adult patients with locally advanced or metastatic ROS1-positive non-small cell lung cancer (NSCLC). (1.1)
- adult and pediatric patients 12 years of age and older with solid tumors that:
- have a neurotrophic tyrosine receptor kinase (NTRK) gene fusion and
- are locally advanced or metastatic or where surgical resection is likely to result in severe morbidity.
- have progressed following treatment or have no satisfactory alternative therapy.

This indication is approved under accelerated approval based on overall response rate and duration of response. Continued approval for this indication may be contingent upon verification and description of clinical benefit in the confirmatory trials. (1.2)

2 DOSAGE AND ADMINISTRATION

- Select patients for the treatment of locally advanced or metastatic NSCLC based on the presence of ROS1 rearrangement(s) in tumor specimens. (2.1)
- Select patients for treatment of locally advanced or metastatic solid tumors based on the presence of an NTRK gene fusion. (2.1)
- Recommended Dosage: 160 mg orally once daily for 14 days, then increase to 160 mg twice daily, with or without food. (2.4)

3 DOSAGE FORMS AND STRENGTHS

Capsules: 40 mg, 160 mg (3)

4 CONTRAINDICATIONS

None.

5 WARNINGS AND PRECAUTIONS

- Central Nervous System (CNS) Effects: Can cause CNS adverse reactions including dizziness, ataxia, and cognitive impairment. Withhold and then resume at same or reduced dose upon improvement, or permanently discontinue AUGTYRO based on severity. (5.1)
- Interstitial Lung Disease (ILD)/Pneumonitis: Monitor patients for new or worsening pulmonary symptoms indicative of ILD/pneumonitis. Immediately withhold in patients with suspected ILD/pneumonitis and permanently discontinue if ILD/pneumonitis is confirmed. (5.2)
- Hepatotoxicity: Monitor liver function tests every 2 weeks during the first month of treatment, and as clinically indicated thereafter. Based on severity, withhold and then resume at same or reduced dose, or permanently discontinue. (5.3)
- Myalgia with Creatine Phosphokinase (CPK) Elevation: Monitor serum CPK levels during treatment in patients reporting unexplained muscle pain, tenderness, or weakness. Based on severity, withhold and resume at same or reduced dose upon improvement. (5.4)
- Hyperuricemia: Monitor serum uric acid levels prior to initiating and periodically during treatment. Initiate treatment with urate-lowering medications as clinically indicated. Withhold and resume at same or reduced dose, or permanently discontinue based on severity. (5.5)
- Skeletal Fractures: Promptly evaluate patients with signs or symptoms (e.g., pain, changes in mobility, deformity) of fractures. (5.6)
- Embryo-Fetal Toxicity: Can cause fetal harm. Advise females of reproductive potential of the potential risk to a fetus and to use an effective non-hormonal method of contraception. (5.7)

6 ADVERSE REACTIONS

The most common adverse reactions (≥20%) were dizziness, dysgeusia, peripheral neuropathy, constipation, dyspnea, fatigue, ataxia, cognitive impairment, muscular weakness, and nausea. (6.1)

To report SUSPECTED ADVERSE REACTIONS, contact Bristol-Myers Squibb at 1-800-721-5072 or FDA at 1-800-FDA-1088 or www.fda.gov/medwatch.

7 DRUG INTERACTIONS

- Strong and Moderate CYP3A Inhibitors: Avoid concomitant use. (7.1)
- P-gp inhibitors: Avoid concomitant use. (7.1)
- Strong and Moderate CYP3A Inducers: Avoid concomitant use. (7.1)
- Certain CYP3A Substrates: Avoid concomitant use with CYP3A substrates, where minimal concentration changes can cause reduced efficacy. (7.2)
- Hormonal contraceptives: Avoid concomitant use. (7.2)

8 USE IN SPECIFIC POPULATIONS

- Lactation: Advise not to breastfeed. (8.2)

FULL PRESCRIBING INFORMATION

1 INDICATIONS AND USAGE

1.1 ROS1-Positive Non-Small Cell Lung Cancer

AUGTYRO is indicated for the treatment of adult patients with locally advanced or metastatic ROS1-positive non-small cell lung cancer (NSCLC) [see Dosage and Administration (2.1)].

1.2 NTRK Gene Fusion-Positive Solid Tumors

AUGTYRO is indicated for the treatment of adult and pediatric patients 12 years of age and older with solid tumors that:

- have a neurotrophic tyrosine receptor kinase (NTRK) gene fusion [see Dosage and Administration (2.1)],
- are locally advanced or metastatic or where surgical resection is likely to result in severe morbidity, and
- have progressed following treatment or have no satisfactory alternative therapy.

This indication is approved under accelerated approval based on overall response rate and duration of response [see Clinical Studies (14.2)]. Continued approval for this indication may be contingent upon verification and description of clinical benefit in a confirmatory trial(s).

2 DOSAGE AND ADMINISTRATION

2.1 Patient Selection

NSCLC

Select patients for the treatment of locally advanced or metastatic NSCLC with AUGTYRO based on the presence of ROS1 rearrangement(s) in tumor specimens [see Clinical Studies (14.1)]. An FDA-approved test to detect ROS1 rearrangements for selecting patients for treatment with AUGTYRO is not currently available.

Solid Tumors

Select patients for the treatment of solid tumors with AUGTYRO based on the presence of NTRK1/2/3 rearrangements in tumor specimens [see Clinical Studies (14.2)]. An FDA-approved test to detect NTRK1/2/3 rearrangements for selecting patients for treatment with AUGTYRO is not currently available.

- In patients with secretory breast cancer or mammary analogue secretory cancer, consider treatment without confirmation of NTRK rearrangements in tumor specimens.

2.2 Important Information Prior to Initiating AUGTYRO

Prior to initiating AUGTYRO, discontinue strong and moderate CYP3A inhibitors for 3 to 5 elimination half-lives of the CYP3A inhibitor [see Drug Interactions (7.1), Clinical Pharmacology (12.3)].

2.3 Recommended Evaluation and Testing Before Initiating AUGTYRO

Prior to initiation of AUGTYRO, evaluate:

- liver function tests including bilirubin [see Warnings and Precautions (5.3)]
- uric acid level [see Warnings and Precautions (5.5)]

2.4 Recommended Dosage

The recommended dosage of AUGTYRO for adult and pediatric patients 12 years of age and older is 160 mg taken orally once daily with or without food [see Clinical Pharmacology (12.3)] for 14 days, then increase to 160 mg twice daily and continue until disease progression or unacceptable toxicity.

2.5 Dosage Modifications for Adverse Reactions

The recommended dosage reductions of AUGTYRO for the management of adverse reactions are provided in Table 1.

Table 1: Recommended Dose Reductions for AUGTYRO Adverse Reactions
Dose | Dose Reduction
Dose | First | Second
160 mg Once Daily | 120 mg Once Daily | 80 mg Once Daily
160 mg Twice Daily | 120 mg Twice Daily | 80 mg Twice Daily

Recommended dosage modifications of AUGTYRO for the management of adverse reactions are provided in Table 2.

Table 2: Recommended Dosage Modifications for AUGTYRO Adverse Reactions
Adverse Reaction | Severity* | Dosage Modification
Central Nervous System Effects; [see Warnings and Precautions (5.1)] | Intolerable; Grade 2 | - Withhold AUGTYRO until ≤Grade 1 or baseline. - Resume at same or reduced dose, as clinically appropriate.
Central Nervous System Effects; [see Warnings and Precautions (5.1)] | Grade 3 | - Withhold AUGTYRO until ≤Grade 1 or baseline. - Resume at reduced dose.
Central Nervous System Effects; [see Warnings and Precautions (5.1)] | Grade 4 | - Permanently discontinue AUGTYRO.
Interstitial Lung Disease (ILD)/Pneumonitis; [see Warnings and Precautions (5.2)] | Any Grade | - Withhold AUGTYRO if ILD/pneumonitis is suspected. - Permanently discontinue if ILD/pneumonitis is confirmed.
Hepatotoxicity; [see Warnings and Precautions (5.3)] | Grade 3 | - Withhold AUGTYRO until ≤Grade 1 or baseline. - Resume at same dose if resolution occurs within 4 weeks. - Resume at a reduced dose for recurrent Grade 3 events that resolve within 4 weeks.
Hepatotoxicity; [see Warnings and Precautions (5.3)] | Grade 4 | - Withhold AUGTYRO until ≤Grade 1 or baseline. - Resume at reduced dose. - Permanently discontinue if adverse reaction does not resolve within 4 weeks. - Permanently discontinue for recurrent Grade 4 events.
Hepatotoxicity; [see Warnings and Precautions (5.3)] | ALT or AST greater than 3 times ULN with concurrent total bilirubin greater than 1.5 times ULN (in the absence of cholestasis or hemolysis) | - Permanently discontinue AUGTYRO.
Creatine Phosphokinase (CPK) Elevation [see Warnings and Precautions (5.4)] | CPK elevation greater than 5 times ULN | - Withhold until recovery to baseline or to less than or equal to 2.5 times ULN, then resume at same dose.
Creatine Phosphokinase (CPK) Elevation [see Warnings and Precautions (5.4)] | CPK elevation greater than 10 times ULN or second occurrence of CPK elevation of greater than 5 times ULN | - Withhold until recovery to baseline or to less than or equal to 2.5 times ULN, then resume at reduced dose.
Hyperuricemia [see Warnings and Precautions (5.5)] | Grade 3 or Grade 4 | - Withhold AUGTYRO until improvement of signs or symptoms. - Resume AUGTYRO at same or reduced dose.
Other Clinically Relevant Adverse Reactions [see Adverse Reactions (6.1)] | Intolerable; Grade 2 or Grade 3 or Grade 4 | - Withhold AUGTYRO until ≤Grade 1 or baseline. - Resume at the same or reduced dose if resolution occurs within 4 weeks. - Permanently discontinue if adverse reaction does not resolve within 4 weeks. - Permanently discontinue for recurrent Grade 4 events.
*Graded per Common Terminology Criteria for Adverse Events v4.03

2.6 Administration

Take AUGTYRO at approximately the same time each day with or without food [see Pharmacokinetics (12.3)].

Swallow AUGTYRO capsules whole. Do not open, chew, crush, or dissolve the capsule prior to swallowing. Do not take any AUGTYRO capsules that are broken, cracked, or damaged.

If a dose of AUGTYRO is missed or if vomiting occurs at any time after taking a dose, skip the dose and resume AUGTYRO at its regularly scheduled time.

3 DOSAGE FORMS AND STRENGTHS

Capsules: 40 mg, white, opaque, immediate release, Size 0, hard shell capsule, filled with white to off-white powder which may appear as a plug, imprinted with “REP 40” in blue text on the cap.

Capsules: 160 mg, blue, opaque, immediate release, Size 0, hard shell capsule, filled with white to off-white powder which may appear as a plug, imprinted with “REP 160” in white text on the cap.

4 CONTRAINDICATIONS

None.

5 WARNINGS AND PRECAUTIONS

5.1 Central Nervous System Adverse Reactions

AUGTYRO can cause central nervous system adverse reactions.

Among the 426 patients who received AUGTYRO in Study TRIDENT-1, a broad spectrum of central nervous system (CNS) adverse reactions including dizziness, ataxia, and cognitive disorders occurred in 77% of patients, with Grade 3 or 4 events occurring in 4.5% of patients.

Dizziness, including vertigo, occurred in 65% of patients; Grade 3 dizziness occurred in 2.8% of patients. The median time to onset was 7 days (1 day to 1.4 years). Dose interruption was required in 9% of patients, and 11% required dose reduction of AUGTYRO due to dizziness.

Ataxia, including gait disturbance and balance disorder, occurred in 28% of patients; Grade 3 ataxia occurred in 0.5% of patients. The median time to onset was 15 days (1 day to 1.4 years). Dose interruption was required in 5% of patients, 8% required dose reduction, and one patient (0.2%) permanently discontinued AUGTYRO due to ataxia.

Cognitive impairment, including memory impairment and disturbance in attention, occurred in 25% of patients. Cognitive impairment included memory impairment (15%), disturbance in attention (12%), and confusional state (2%); Grade 3 cognitive impairment occurred in 0.9% of patients. The median time to onset of cognitive disorders was 37 days (1 day to 1.4 years). Dose interruption was required in 2% of patients, 2.1% required dose reduction, and 0.5% patients permanently discontinued AUGTYRO due to cognitive adverse reactions.

Mood disorders occurred in 6% of patients. Mood disorders occurring in > 1% of patients included anxiety (2.6%); Grade 4 mood disorders (mania) occurred in 0.2% of patients. Dose interruption was required in 0.2% of patients and 0.2% of patients required a dose reduction due to mood disorders.

Sleep disorders including insomnia and hypersomnia occurred in 18% of patients. Sleep disorders observed in > 1% of patients were somnolence (9%), insomnia (6%) and hypersomnia (1.6%). Dose interruption was required in 0.7% of patients, and 0.2% of patients required a dose reduction due to sleep disorders.

The incidences of CNS adverse reactions observed were similar in patients with and without CNS metastases.

Advise patients and caregivers of the risk of CNS adverse reactions with AUGTYRO. Advise patients not to drive or use machines if they are experiencing CNS adverse reactions. Withhold and then resume at same or reduced dose upon improvement, or permanently discontinue AUGTYRO based on severity [see Dosage and Administration (2.5)].

5.2 Interstitial Lung Disease/Pneumonitis

AUGTYRO can cause interstitial lung disease (ILD)/pneumonitis.

Among the 426 patients treated with AUGTYRO, ILD/pneumonitis (pneumonitis [2.8%] and ILD [0.2%]) occurred in 3.1% of patients; Grade 3 ILD/pneumonitis occurred in 1.2% of patients. The median time to onset was 45 days (19 days to 0.9 years). Dose interruption was required in 1.4% of patients, 0.5% of patients required dose reduction, and 1.1% of patients permanently discontinued AUGTYRO due to ILD/pneumonitis.

Monitor patients for new or worsening pulmonary symptoms indicative of ILD/pneumonitis. Immediately withhold AUGTYRO in patients with suspected ILD/pneumonitis and permanently discontinue AUGTYRO if ILD/pneumonitis is confirmed [see Dosage and Administration (2.5)].

5.3 Hepatotoxicity

AUGTYRO can cause hepatotoxicity.

Among the 426 patients treated with AUGTYRO, increased alanine transaminase (ALT) occurred in 38%, increased aspartate aminotransferase (AST) occurred in 41%, including Grade 3 or 4 increased ALT in 3.3% and increased AST in 2.9%. The median time to onset of increased ALT or AST was 15 days (range: 1 day to 1.9 years). Increased ALT or AST leading to dose interruptions or reductions occurred in 2.8% and 1.2% of patients, respectively. Hyperbilirubinemia leading to dose interruptions occurred in 0.5%.

Monitor liver function tests, including ALT, AST and bilirubin, every 2 weeks during the first month of treatment, then monthly thereafter and as clinically indicated. Withhold and then resume at the same or reduced dose upon improvement, or permanently discontinue AUGTYRO based on the severity [see Dosage and Administration (2.5)].

5.4 Myalgia with Creatine Phosphokinase Elevation

AUGTYRO can cause myalgia with or without creatine phosphokinase (CPK) elevation.

Among the 426 patients treated with AUGTYRO, myalgia occurred in 13% of patients, with Grade 3 in 0.7%. Median time to onset of myalgia was 19 days (range: 1 day to 2 years). Concurrent increased CPK within a 7-day window was observed in 3.7% of patients. AUGTYRO was interrupted in one patient with myalgia and concurrent CPK elevation.

Advise patients to report any unexplained muscle pain, tenderness, or weakness.

Monitor serum CPK levels during AUGTYRO treatment and monitor CPK levels every 2 weeks during the first month of treatment and as needed in patients reporting unexplained muscle pain, tenderness, or weakness. Initiate supportive care as clinically indicated. Based on severity, withhold and then resume AUGTYRO at the same or reduced dose upon improvement [see Dosage and Administration (2.5)].

5.5 Hyperuricemia

AUGTYRO can cause hyperuricemia.

Among the 426 patients treated with AUGTYRO, 21 patients (5%) experienced hyperuricemia reported as an adverse reaction and 0.7% of patients experienced Grade 3 or 4 hyperuricemia. One patient without pre-existing gout required urate-lowering medication.

Monitor serum uric acid levels prior to initiating AUGTYRO and periodically during treatment. Initiate treatment with urate-lowering medications as clinically indicated. Withhold and then resume at the same or reduced dose upon improvement, or permanently discontinue AUGTYRO based on severity [see Dosage and Administration (2.5)].

5.6 Skeletal Fractures

AUGTYRO can cause skeletal fractures.

Among 426 adult patients who received AUGTYRO, fractures occurred in 2.3%. Fractures involved the ribs (0.5%), feet (0.5%), spine (0.2%), acetabulum (0.2%), sternum (0.2%), and ankles (0.2%). Some fractures occurred at sites of disease and prior radiation therapy. The median time to fracture was 71 days (range: 31 days to 1.4 years). AUGTYRO was interrupted in 0.3% of patients.

Of 26 evaluable patients in an ongoing open-label study in pediatric patients, fractures occurred in one 12-year-old patient (ankle/foot) and one 10-year-old patient (stress fracture). AUGTYRO was interrupted in both patients. AUGTYRO is not approved for use in pediatric patients less than 12 years of age [see Pediatric Use (8.4)].

Promptly evaluate patients with signs or symptoms (e.g., pain, changes in mobility, deformity) of fractures. There are no data on the effects of AUGTYRO on healing of known fractures and risk of future fractures.

5.7 Embryo-Fetal Toxicity

Based on literature reports in humans with congenital mutations leading to changes in tropomyosin receptor tyrosine kinase (TRK) signaling, findings from animal studies, and its mechanism of action, AUGTYRO can cause fetal harm when administered to a pregnant woman.

Oral administration of repotrectinib to pregnant rats during the period of organogenesis resulted in fetal malformations at doses approximately 0.3 times the recommended 160 mg twice daily dose based on body surface area (BSA).

Advise pregnant women of the potential risk to a fetus. Advise females of reproductive potential to use effective non-hormonal contraception during treatment with AUGTYRO and for 2 months following the last dose, since AUGTYRO can render some hormonal contraceptives ineffective [see Drug Interactions (7.2)].Advise male patients with female partners of reproductive potential to use effective contraception during treatment with AUGTYRO and for 4 months after the last dose [see Use in Specific Populations (8.1, 8.3)].

6 ADVERSE REACTIONS

The following clinically significant adverse reactions are described elsewhere in the labeling:

- Central Nervous System Adverse Reactions [see Warnings and Precautions (5.1)]
- Interstitial Lung Disease (ILD)/Pneumonitis [see Warnings and Precautions (5.2)]
- Hepatotoxicity [see Warnings and Precautions (5.3)]
- Myalgia with Creatine Phosphokinase Elevation [see Warnings and Precautions (5.4)]
- Hyperuricemia [see Warnings and Precautions (5.5)]
- Skeletal Fractures [see Warnings and Precautions (5.6)]
- Embryo-Fetal Toxicity [see Warnings and Precautions (5.7)]

6.1 Clinical Trials Experience

Because clinical trials are conducted under widely varying conditions, adverse reaction rates reported in the clinical trials of a drug cannot be directly compared to rates in the clinical trials of another drug and may not reflect the rates observed in practice.

The pooled safety population described in WARNINGS AND PRECAUTIONS and below reflects exposure to AUGTYRO in 426 patients with ROS1-positive NSCLC (n=320), NTRK1/2/3-positive solid tumors (n=104), or other solid tumors (n=2) in TRIDENT-1. Patients received AUGTYRO at a dose of 160 mg orally once daily for the first 14 days, then increased to 160 mg orally twice daily until disease progression or unacceptable toxicity [see Clinical Studies (14.1), (14.2)]. Eligible patients had an ECOG status of ≤1. Patients with a history of ILD, drug-related pneumonitis, significant, uncontrolled, active cardiovascular disease, or prolonged QTc interval were excluded from enrollment in this trial. Forty-eight percent of patients were exposed to AUGTYRO for at least 6 months, and 28% were exposed for greater than 1 year.

The median age of patients who received AUGTYRO was 57 years (range: 18 to 93); 59% female; 43% White, 47% Asian, 2.8% Black, 0.5% Native Hawaiian or Other Pacific Islander, 0.5% American Indian or Alaska Native, 6.1% race not reported or other, and 0.7% unknown.

Serious adverse reactions occurred in 35% of patients who received AUGTYRO. Serious adverse reactions in ≥2% of patients included pneumonia (6.3%), dyspnea (3.1%), pleural effusion (2.8%), and hypoxia (2.6%). Fatal adverse reactions occurred in 3.5% of patients who received AUGTYRO, including pneumonia, pneumonia aspiration, cardiac arrest, sudden cardiac death, cardiac failure, hypoxia, dyspnea, respiratory failure, tremor, and disseminated intravascular coagulation.

Permanent discontinuation of AUGTYRO due to an adverse reaction occurred in 7% of patients. There were no specific adverse reactions that accounted for ≥1% of permanent discontinuations.

Dosage interruptions of AUGTYRO due to an adverse reaction occurred in 50% of patients. Adverse reactions that required dosage interruption in ≥2% of patients were dizziness, dyspnea, muscular weakness, ataxia, pneumonia, peripheral neuropathy, anemia, and vomiting.

Dose reductions of AUGTYRO due to an adverse reaction occurred in 38% of patients. Adverse reactions that required dosage reductions in ≥2% of patients included dizziness, ataxia, muscular weakness, peripheral neuropathy, and cognitive impairment.

The most common (≥20%) adverse reactions that occurred in patients receiving AUGTYRO were dizziness, dysgeusia, peripheral neuropathy, constipation, dyspnea, fatigue, ataxia, cognitive impairment, muscular weakness and nausea.

Table 3 summarizes the adverse reactions that occurred in TRIDENT-1.

Table 3: Adverse Reactions (≥10%) in Patients with ROS1-Positive NSCLC or NTRK-Positive Solid Tumors Who Received AUGTYRO in TRIDENT-1
Adverse Reaction^1 | AUGTYRO; N=426
Adverse Reaction^1 | All Grades (%) | Grade 3 or 4 (%)
Nervous System Disorders
Dizzinessa | 65 | 2.8
Dysgeusiab | 54 | 0
Peripheral neuropathyc | 49 | 1.4
Ataxiad | 28 | 0.5
Cognitive impairmente | 25 | 0.9
Headachef | 19 | 0
Gastrointestinal Disorders
Constipation | 38 | 0.2
Nausea | 20 | 0.7
Diarrhea | 14 | 0.7
Vomiting | 12 | 1.2
Respiratory, Thoracic, and Mediastinal Disorders
Dyspneag | 30 | 6
Coughh | 18 | 0.2
Pneumoniai | 11 | 6
General Disorders
Fatiguej | 30 | 1.2
Edemak | 15 | 0.5
Decreased appetite | 11 | 0.2
Musculoskeletal and Connective Tissue Disorders
Muscular weakness | 20 | 2
Myalgial | 13 | 0.7
Metabolism and Nutritional
Increased weight | 16 | 3
Eye Disorders
Vision disordersm | 12 | 0.5
^1 Based on NCI CTCAE v4.03
a Includes terms dizziness, vertigo, dizziness postural, dizziness exertional, vertigo positional
b Includes terms dysgeusia, ageusia, anosmia, hypogeusia
c Includes terms neuralgia, neuropathy peripheral, peripheral sensory neuropathy, dysesthesia, peripheral motor neuropathy, polyneuropathy, paresthesia, hypoesthesia, hyperesthesia
d Includes terms ataxia, gait disturbance, balance disorder, cerebellar ataxia and coordination abnormal
e Includes terms memory impairment, disturbance in attention, cognitive disorder, confusional state, amnesia, attention deficit hyperactivity disorder, delirium, altered state of consciousness, aphasia, delusion, depressed level of consciousness, hallucination, mental status changes, neurological decompensation
f Includes terms headache, migraine, tension headache
g Includes terms dyspnea and dyspnea exertional
h Includes terms productive cough, cough, and upper-airway cough syndrome
i Includes terms pneumonia, pneumonia aspiration, lower respiratory tract infection, pneumonia viral, pneumonia bacterial, lower respiratory tract infection bacterial, pneumonia klebsiella
j Includes terms fatigue and asthenia
k Includes terms generalized edema, periorbital edema, localized edema, face edema, edema peripheral, edema, eye edema, scrotal edema
l Includes terms myalgia, myositis, musculoskeletal discomfort, musculoskeletal pain
m Includes terms vision blurred, dry eye, visual impairment, visual field defect, cataract, conjunctivitis, eye pain, photophobia, photosensitivity reaction, visual acuity reduced, vitreous floaters, blepharospasm, color blindness, diplopia, eye hematoma, eye swelling, eyelid disorder, eyelid injury, eyelids pruritus, glaucoma, night blindness, ophthalmic herpes zoster

Clinically relevant adverse reactions occurring in <10% of patients receiving AUGTYRO were pyrexia (9.2%) and fall (3.8%).

Table 4 summarizes the laboratory abnormalities in TRIDENT-1.

Table 4: Laboratory Abnormalities (≥20%) that Worsened from Baseline in Patients with ROS1-Positive NSCLC or NTRK-Positive Solid Tumors Who Received AUGTYRO in TRIDENT-1
Laboratory Abnormality^1 | AUGTYRO^2 N=426
Laboratory Abnormality^1 | All Grades (%) | Grade 3 or 4 (%)
Hematology
Decreased hemoglobin | 79 | 8.4
Decreased lymphocytes | 43 | 10
Decreased neutrophils | 34 | 9
Increased activated partial thromboplastin time | 26 | 0.3
Increased INR | 24 | 0
Chemistry
Increased creatine phosphokinase | 61 | 7
Increased gamma glutamyl transferase | 50 | 13
Increased aspartate aminotransferase | 41 | 2.9
Increased alanine aminotransferase | 38 | 3.3
Increased sodium | 33 | 0.2
Increased alkaline phosphatase | 29 | 2.1
Increased glucose | 26 | 2.4
Increased urate | 23 | 12
Decreased phosphate | 22 | 6
Increased potassium | 22 | 0.7
Decreased glucose | 20 | 0.2
^1 Based on NCI CTCAE v4.03
^2 The denominator used to calculate the rate varied from 233 to 423 based on the number of patients with a baseline value and at least one post-treatment value.

7 DRUG INTERACTIONS

7.1 Effects of Other Drugs on AUGTYRO

Strong and Moderate CYP3A Inhibitors

Avoid concomitant use with strong or moderate CYP3A inhibitors. Concomitant use of AUGTYRO with a strong or a moderate CYP3A inhibitor may increase repotrectinib exposure, which may increase the incidence and severity of adverse reactions of AUGTYRO. Discontinue CYP3A inhibitors for 3 to 5 elimination half-lives of the CYP3A inhibitor prior to initiating AUGTYRO [see Clinical Pharmacology (12.3)].

P-gp Inhibitors

Avoid concomitant use with P-gp inhibitors. Concomitant use of AUGTYRO with a P-gp inhibitor may increase repotrectinib exposure, which may increase the incidence and severity of adverse reactions of AUGTYRO [see Clinical Pharmacology (12.3)].

Strong and Moderate CYP3A Inducers

Avoid concomitant use with strong or moderate CYP3A inducers. Concomitant use of AUGTYRO with a strong or moderate CYP3A inducer may decrease repotrectinib plasma concentrations, which may decrease efficacy of AUGTYRO [see Clinical Pharmacology (12.3)].

7.2 Effects of AUGTYRO on Other Drugs

Certain CYP3A4 Substrates

Avoid concomitant use unless otherwise recommended in the Prescribing Information for CYP3A substrates, where minimal concentration changes can cause reduced efficacy. If concomitant use is unavoidable, increase the CYP3A4 substrate dosage in accordance with approved product labeling.

Repotrectinib is a CYP3A4 inducer. Concomitant use of repotrectinib decreases the concentration of CYP3A4 substrates [see Clinical Pharmacology (12.3)], which can reduce the efficacy of these substrates.

Contraceptives

Repotrectinib is a CYP3A4 inducer, which can decrease progestin or estrogen exposure to an extent that could reduce the effectiveness of hormonal contraceptives.

Avoid concomitant use of AUGTYRO with hormonal contraceptives [see Use in Specific Populations (8.1, 8.3)]. Advise females of reproductive potential to use an effective nonhormonal contraceptive [see Use in Specific Populations (8.1, 8.3)].

8 USE IN SPECIFIC POPULATIONS

8.1 Pregnancy

Risk Summary

Based on literature reports in humans with congenital mutations leading to changes in TRK signaling, findings from animal studies, and its mechanism of action [see Clinical Pharmacology (12.1)], AUGTYRO can cause fetal harm when administered to a pregnant woman. There are no available data on AUGTYRO use in pregnant women. Oral administration of repotrectinib to pregnant rats during the period of organogenesis resulted in fetal malformations at doses approximately 0.3 times the recommended dose of 160 mg twice daily based on BSA (see Data). Advise pregnant women of the potential risk to a fetus.

In the U.S. general population, the estimated background risk of major birth defects and miscarriage in clinically recognized pregnancies is 2% to 4% and 15% to 20%, respectively.

Data

Human Data

Published reports of individuals with congenital mutations in TRK pathway proteins suggest that decreases in TRK-mediated signaling are correlated with obesity, developmental delays, cognitive impairment, insensitivity to pain, and anhidrosis.

Animal Data

In an embryo-fetal development study, once daily oral administration of repotrectinib to pregnant rats during the period of organogenesis from gestation day 6 to 17 resulted in maternal effects of increased body weight and skin abrasions/ulcerations at doses ≥6 mg/kg, fetal malformations of malrotated hindlimbs and lower fetal body weights at doses ≥12 mg/kg [approximately 0.3 times the recommended dose of 160 mg twice daily based on BSA]. No embryolethality was observed.

8.2 Lactation

Risk Summary

There are no data on the presence of AUGTYRO in human milk or its effects on either the breastfed child or on milk production. Because of the potential for serious adverse reactions in breastfed children from AUGTYRO, advise a lactating woman to discontinue breastfeeding during treatment with AUGTYRO and for 10 days after the last dose.

8.3 Females and Males of Reproductive Potential

AUGTYRO can cause fetal harm when administered to a pregnant woman [see Use in Specific Populations (8.1)].

Pregnancy Testing

Verify the pregnancy status of females of childbearing potential prior to initiating AUGTYRO [see Use in Specific Populations (8.1)].

Contraception

AUGTYRO can cause embryo-fetal harm when administered to a pregnant woman [see Use in Specific Populations (8.1)].

Females

Advise females of childbearing potential to use effective non-hormonal contraception during treatment with AUGTYRO and for 2 months following the last dose. AUGTYRO can render some hormonal contraceptives ineffective [see Drug Interactions (7.2)].

Males

Based on genotoxicity findings, advise male patients with female partners of childbearing potential to use effective contraception during treatment with AUGTYRO and for 4 months following the last dose [see Nonclinical Toxicology (13.1)].

8.4 Pediatric Use

The safety and effectiveness of AUGTYRO in pediatric patients with ROS1-positive NSCLC have not been established.

The safety and effectiveness of AUGTYRO have not been established in pediatric patients younger than 12 years of age with solid tumors who have an NTRK gene fusion.

The safety and effectiveness of AUGTYRO for the treatment of locally advanced or metastatic NTRK-positive solid tumors have been established in pediatric patients 12 years of age or older. Use of AUGTYRO in this age group is supported by evidence from an adequate and well-controlled study in adult patients with additional pharmacokinetic and safety data in pediatric patients aged 12 years and older. This includes data demonstrating that the exposure of repotrectinib in pediatric patients 12 years of age and older is expected to result in similar safety and efficacy to that of adults, and that the course of locally advanced or metastatic NTRK-positive solid tumors is sufficiently similar in adults and pediatric patients 12 years of age or older to allow extrapolation of data in adult to pediatric patients 12 years of age or older [see Dosage and Administration (2.4), Warnings and Precautions (5.7), Adverse Reactions (6.1) and Clinical Pharmacology (12.3)].

Juvenile Animal Data

Daily oral administration of repotrectinib to juvenile rats for 8 weeks starting on postnatal day 12 (approximately equal to a human pediatric age of a newborn) resulted in toxicities similar to those observed in adult rats, though juvenile animals showed decreased body weight gain at doses ≥1 mg/kg (approximately ≥0.04 times the human exposure based on AUC at the recommended clinical dose of 160 mg BID) and decreased femur lengths at 3 mg/kg (approximately 0.1 times the human exposure based on AUC at the recommended clinical dose of 160 mg BID). Decreased body weight gain and decreased femur lengths persisted following 4 weeks of recovery.

8.5 Geriatric Use

Of the 426 patients who received AUGTYRO, in the TRIDENT-1 study for ROS1-positive non-small cell lung cancer or NTRK gene fusion-positive solid tumors, 19% were 65 to 75 years old, and 6% were 75 years of age or older. There were no clinically meaningful differences in safety and efficacy between patients younger than 65 years of age and patients 65 years of age or older.

8.6 Renal Impairment

The recommended dosage of AUGTYRO has not been established in patients with severe renal impairment or kidney failure (eGFR <30 mL/min) and patients on dialysis [see Clinical Pharmacology (12.3)].

No dosage modification is recommended for patients with mild or moderate renal impairment (eGFR 30 to 90 mL/min).

8.7 Hepatic Impairment

The recommended dosage of AUGTYRO has not been established in patients with moderate (total bilirubin >1.5 to 3 times upper limit of normal [ULN] with any AST) or severe (total bilirubin >3 times ULN with any AST) hepatic impairment [see Clinical Pharmacology (12.3)].

No dosage modification is recommended for patients with mild (total bilirubin >1 to 1.5 times ULN or AST > ULN) hepatic impairment.

11 DESCRIPTION

Repotrectinib is a kinase inhibitor. The molecular formula for repotrectinib is C18H18FN5O2 and the molecular weight is 355.37 Daltons. The chemical name is (3R,11S)-6-Fluoro-3,11-dimethyl-10-oxa-2,13,17,18,21-pentaazatetracyclo[13.5.2.0^4,9.0^18,22]docosa-1(21),4,6,8,15(22),16,19-heptaen-14-one. The chemical structure of repotrectinib is as follows:

Repotrectinib is a white to off-white powder.

AUGTYRO (repotrectinib) capsules for oral use are supplied as printed hard shell capsules containing 40 mg of repotrectinib. Inactive ingredients are microcrystalline cellulose, sodium lauryl sulfate, croscarmellose sodium, and colloidal silicon dioxide.

The white opaque capsule shell contains gelatin and titanium dioxide. The printing ink contains shellac and FD & C blue #2 aluminum lake.

AUGTYRO (repotrectinib) capsules for oral use are supplied as printed hard shell capsules containing 160 mg of repotrectinib. Inactive ingredients are microcrystalline cellulose, sodium lauryl sulfate, croscarmellose sodium, magnesium stearate, and colloidal silicon dioxide.

The blue opaque capsule shell contains gelatin, titanium dioxide and FD & C blue #1. The printing ink contains shellac and titanium dioxide.

12 CLINICAL PHARMACOLOGY

12.1 Mechanism of Action

Repotrectinib is an inhibitor of proto-oncogene tyrosine-protein kinase ROS1 (ROS1) and of the tropomyosin receptor tyrosine kinases (TRKs) TRKA, TRKB, and TRKC.

Fusion proteins that include ROS1 or TRK domains can drive tumorigenic potential through hyperactivation of downstream signaling pathways leading to unconstrained cell proliferation. Repotrectinib exhibited anti-tumor activity in cultured cells expressing ROS1 fusions and mutations including SDC4-ROS1, SDC4-ROS1G2032R, CD74-ROS1, CD74-ROS1G2032R, CD74-ROS1D2033N, and CD74-ROS1L2026M. Repotrectinib also inhibited cell proliferation in cultured cells expressing NTRK fusions and mutations including LMNA-TRKA, LMNA-TRKAG595R, EVT6-TRKBG639R, and ETV6-TRKCG623R.

12.2 Pharmacodynamics

Repotrectinib exposure-response relationships and the time course of pharmacodynamic responses are not fully characterized.

Cardiac Electrophysiology

AUGTYRO does not cause a mean increase in the QTc interval > 20 milliseconds (ms) at 160 mg QD followed by 160 mg BID, the approved recommended dosage.

12.3 Pharmacokinetics

The geometric mean (CV%) of repotrectinib steady state peak concentration (Cmax,ss) is 713 (32.5%) ng/mL and the area under the time concentration curve (AUC0-24h,ss) is 7210 (40.1%) ng•h/mL following the approved recommended twice daily dosage in patients with cancer. Repotrectinib Cmax and AUC0-inf increases approximately dose proportional (but less than linear with estimated slopes of 0.78 and 0.70, respectively) over the single dose range of 40 mg to 240 mg (0.25 to 1.5 times the approved recommended dosage). Steady state PK was time-dependent with an autoinduction of CYP3A4. Steady state is achieved within 14 days of daily administration of 160 mg.

Absorption

The geometric mean (CV%) absolute bioavailability of repotrectinib is 45.7% (19.6%). Peak repotrectinib concentration occurred at approximately 2 to 3 hours post a single oral dose of 40 mg to 240 mg (0.25 to 1.5 times the approved recommended dosage) under fasted conditions.

Effect of Food

No clinically significant differences in repotrectinib pharmacokinetics were observed in patients with cancer following administration of a high-fat meal (approximately 800-1000 calories, 50% fat).

Distribution

The geometric mean (CV%) apparent volume of distribution (Vz/F) was 432 L (55.9 %) in patients with cancer following a single 160 mg oral dose of AUGTYRO.

AUGTYRO binding to plasma protein was 95.4% invitro. The blood-to-plasma ratio was 0.56 in vitro.

Elimination

Repotrectinib elimination is time-dependent due to autoinduction of CYP3A4.

The repotrectinib mean terminal half-life is approximately 60.7 h for patients with cancer following a single dose. The steady state repotrectinib terminal half-life is approximately 40.3 h for patients with cancer.

The geometric mean (CV%) apparent oral clearance (CL/F) was 15.9 L/h (45.5%) in patients with cancer following a single 160 mg oral dose of AUGTYRO.

Metabolism

Repotrectinib is primarily metabolized by CYP3A4 followed by secondary glucuronidation.

Excretion

Following a single oral 160 mg dose of radiolabeled repotrectinib, 4.84% (0.56% as unchanged) was recovered in urine and 88.8% (50.6% unchanged) in feces.

Specific Populations

No clinically significant differences in the pharmacokinetics of repotrectinib were observed based on age (12 to 93 years), sex, race (White 50%, Asian 38%, Black 7%), mild to moderate renal impairment (eGFR 30 to < 90 mL/min), or mild hepatic impairment (total bilirubin >1 to 1.5 times ULN or AST > ULN). The effect of moderate (total bilirubin >1.5 to 3 times ULN with any AST) or severe (total bilirubin >3 x ULN with any AST) hepatic impairment, severe renal impairment, kidney failure (eGFR < 30 mL/min), or dialysis on repotrectinib pharmacokinetics is unknown or not fully characterized.

Drug Interaction Studies

Clinical Studies

Strong CYP3A and P-gp inhibitors: Repotrectinib AUC0-inf increased by 5.9-fold and Cmax by 1.7-fold following concomitant use with itraconazole (strong CYP3A and P-gp inhibitor).

Strong CYP3A and P-gp inducers: Repotrectinib AUC0-inf decreased by 92% and Cmax by 79% following concomitant use with rifampin (strong CYP3A and P-gp inducer).

CYP3A substrates: Midazolam (CYP3A substrate AUC0-inf decreased by 69% and Cmax by 48% following concomitant use in subjects who were previously administered 160 mg repotrectinib once daily for 14 days followed by 160 mg twice daily for 7 days.

In vitro Studies

CYP Enzymes: Repotrectinib induces CYP3A4, CYP2B6, CYP2C8, CYP2C19, CYP2C9 and inhibits CYP3A4/5 (GI tract). Repotrectinib does not induce CYP1A2.

Other Metabolic Pathways: Repotrectinib inhibits UGT1A1.

Transporter Systems: Repotrectinib inhibits P-gp, BCRP, OATP1B1, and MATE2-K. Repotrectinib is a substrate for P-gp.

13 NONCLINICAL TOXICOLOGY

13.1 Carcinogenesis, Mutagenesis, Impairment of Fertility

Carcinogenicity studies with repotrectinib were not conducted.

Repotrectinib was genotoxic in an in vitro assay in human lymphoblastoid TK6 cells and in an in vivo rat bone marrow micronucleus assay via an aneugenic mechanism of action. Repotrectinib was not mutagenic in vitro in the bacterial reverse mutation (Ames) assay.

Dedicated fertility studies were not conducted with repotrectinib. There were no effects on male and female reproductive organs observed in general repeat-dose toxicology studies of up to 3 months in duration in rats and monkeys at any dose level tested, which equated to exposures of up to approximately 3 times the human exposure at the 160 mg twice daily dose based on AUC.

14 CLINICAL STUDIES

14.1 Locally Advanced or Metastatic ROS1-Positive NSCLC

The efficacy of AUGTYRO was evaluated in TRIDENT-1, a multicenter, single-arm, open-label, multi-cohort clinical trial (NCT03093116). Patients were required to have ROS1-positive locally advanced or metastatic NSCLC, ECOG performance status ≤1, measurable disease per RECIST v 1.1, and ≥8 months from first dose. All patients were assessed for CNS lesions at baseline, and patients with symptomatic brain metastases were excluded from the trial. Patients received AUGTYRO 160 mg orally once daily for 14 days, then increased to 160 mg twice daily until disease progression or unacceptable toxicity. Tumor assessments were performed at least every 8 weeks. Identification of ROS1 gene fusions in tumor specimens was prospectively determined in local laboratories using next-generation sequencing (NGS), polymerase chain reaction (PCR) or fluorescence in situ hybridization (FISH) tests. All ROS1-positive patients by local FISH testing required central laboratory confirmation of ROS1 fusion using an analytically validated NGS test. ROS1 fusions were identified by NGS in 51%, FISH in 26%, and PCR in 23%. The major efficacy outcome measures were overall response rate (ORR) and duration of response (DOR) according to RECIST v1.1 as assessed by blinded independent central review (BICR). Intracranial response according to modified RECIST v1.1 was assessed by BICR. Tumor assessments with imaging were performed every 8 weeks. The efficacy populations included 71 ROS1 TKI-naïve patients who received up to 1 prior line of platinum-based chemotherapy and/or immunotherapy and 56 patients who received 1 prior ROS1 TKI with no prior platinum-based chemotherapy or immunotherapy.

Among the 71 ROS1 TKI-naïve patients, the median age was 57 years (range: 28 to 80); female (60.6%); Asian (67.6%), White (25.4%), Hispanic or Latino (4.2%), Black or African American (1.4%); never smoked (63.4%); and ECOG performance status of 1 at baseline (66.2%). At baseline, 94.4% of patients had metastatic disease, 25.4% of patients had CNS metastases by BICR; 97.2% had adenocarcinoma; and 28.2% patients had prior chemotherapy consisting of platinum-based chemotherapy and/or immunotherapy for locally advanced or metastatic disease.

Among the 56 patients who had received 1 prior ROS1 TKI (including crizotinib [82%] and entrectinib [16%]) with no prior platinum-based chemotherapy or immunotherapy, the median age was 57 years (range: 33 – 78); female (67.9%); Asian (48.2%), White (44.6%), Black or African American and Hispanic or Latino (1.8% each); never smoked (64.3%); and ECOG performance status of 1 at baseline (67.9%). At baseline, 98.2% patients had metastatic disease, 42.9% with CNS metastases by BICR, and 94.6% had adenocarcinoma.

Efficacy results are summarized in Table 5.

Table 5: Efficacy Results for Patients with ROS1-Positive NSCLC in TRIDENT-1
Efficacy Parameters | ROS1 Inhibitor Naïve Patients; (N=71) | ROS1 Inhibitor Pretreated Patients; (N=56)
Confirmed Overall Response Rate, % (95% CI) | 79% (68, 88) | 38% (25, 52)
Complete Response | 6% | 5%
Partial Response | 73% | 32%
Duration of Response (DOR)a
Median in Months (95% CI)b | 34.1 (25.6, NE) | 14.8 (7.6, NE)
Range (months) | 1.4+, 42.4+ | 3.6, 22.9+
% DOR ≥12 monthsc | 70 | 48
Abbreviations: CI = confidence interval; NE = not evaluable; “+” indicates ongoing response
a DOR results are based on the updated data as of 19 December 2022.
b Median DOR (95% CI) are based on Kaplan-Meier estimates.
c DOR landmark analysis is based on the observed DOR.

Among TKI-naïve patients, 8 had measurable CNS metastases at baseline as assessed by BICR; responses in intracranial lesions were observed in 7 of these 8 patients. Among the TKI pretreated patients with no prior platinum-based chemotherapy, 12 had measurable CNS metastases at baseline as assessed by BICR; responses in intracranial lesions were observed in 5 of these 12 patients.

Among the 56 ROS1 inhibitor-pretreated patients, 8 had resistance mutations following TKI therapy. Responses were observed in 6 of these 8 patients; responders included patients with solvent front (ROS1G2032R), gatekeeper (ROS1L2026M), and other mutations (ROS1S1986F/Y).

14.2 Locally Advanced or Metastatic NTRK Gene Fusion-Positive Solid Tumors

The efficacy of AUGTYRO was evaluated in TRIDENT-1 (NCT03093116), a multi-center, single-arm, open-label, multi-cohort clinical trial in 88 adult patients with locally advanced or metastatic NTRK gene fusion-positive (NTRK1/2/3) solid tumors who had either received a prior TKI treatment or were TKI-naïve. All patients were assessed for CNS lesions at baseline, and patients with symptomatic brain metastases were excluded from the trial. Patients received AUGTYRO 160 mg orally once daily for 14 days, then increased to 160 mg twice daily until disease progression or unacceptable toxicity. Tumor assessments were performed every 8 weeks. NTRK gene fusions were identified prospectively using NGS in 94%, FISH in 5%, and PCR in 1%. NTRK gene fusion-positive tumors identified by local FISH testing required central laboratory confirmation using an analytically validated NGS test. The major efficacy outcome measures were ORR and DOR according to RECIST v1.1 as assessed by BICR. Intracranial response according to modified RECIST v1.1 was assessed by BICR.

Among the 40 TRK TKI-naïve patients, the median age was 61 years (range: 25 to 84); 60% were female patients; race was Asian 53%, White 25%, Black or African American 5%, and other or not reported 18%; ethnicity was Hispanic or Latino 5%, not Hispanic or Latino 87%, and not reported 8%; and ECOG performance status of 1 at baseline was 55%. At baseline, 98% of patients had metastatic disease and 23% of patients had CNS metastases by BICR. Seventy percent (n=28) of patients received prior systemic therapy with a median of one prior systemic regimen, and 7.5% (n=3) received three or more prior systemic regimens.

Among the 48 TRK TKI-pretreated patients, the median age was 58 years (range: 20 to 81); 48% were female patients; race was White 65%, Asian 25%, Black or African American 2%, and not reported 8%; ethnicity was not Hispanic or Latino 92%, and missing 8%; and ECOG performance status of 1 at baseline was 60%. At baseline, 96% of patients had metastatic disease and 25% of patients had CNS metastases by BICR. Seventy-seven percent (n=37) of patients received 2 or more prior systemic regimens, and 46% (n=22) received three or more prior systemic regimens, and 7 patients (15%) received 2 prior TKI therapies.

Efficacy results are summarized in Table 6.

Table 6: Efficacy Results for Patients with NTRK Gene Fusion-Positive Tumors in TRIDENT-1
Efficacy Parameters | TKI-Naïve Patients; (n=40) | TKI-Pretreated Patients; (n=48)
Confirmed Overall Response Rate, % (95% CI) | 58; (41, 73) | 50; (35, 65)
Complete Response, % | 15 | 0
Partial Response, % | 43 | 50
Median Duration of Response (mDOR)a,; in Months (95% CI) | NE; (NE, NE) | 9.9; (7.4, 13.0)
Range (months) | 3.7+, 43.9+ | 1.8, 26.5+
% with DOR ≥ 6 monthsb | 87 | 71
% with DOR ≥ 9 monthsb | 83 | 63
% with DOR ≥ 12 monthsb | 83 | 42
NE = not evaluable; “+” indicates ongoing response
a Median DOR (95% CI) are based on Kaplan-Meier estimates.
b DOR landmark analysis is based on the observed DOR.

Among the 88 patients, 5 had measurable CNS metastases at baseline as assessed by BICR. Responses were seen in 2 (100%) TKI-naïve patients and 3 (100%) TKI-pretreated patients. One out of 2 TKI-naïve and 2 out of 3 TKI-pretreated patients received prior radiotherapy to the brain, all more than 2 months prior to study entry.

Twenty-six of the TRK TKI-pretreated patients had a resistance mutation at baseline, including 24 with solvent front mutations (NTRK1G595R and NTRK3G623L/R/E/V mutations), one with both a solvent front mutation and a gatekeeper mutation (NTRK1F589L), and one with another mutation (NTRK1G667C). In the 25 TKI-pretreated patients with solvent front mutations at baseline, ORR was 60% (95% CI: 39, 79).

ORR and DOR by tumor type in adult patients with NTRK gene fusion-positive solid tumors are presented in Tables 7 and 8 below.

Table 7: Efficacy Results by Tumor Type in TKI-naïve NTRK Gene Fusion Patients
Tumor type | Patients (n=40) | ORR |  | DOR
Tumor type | Patients (n=40) | n (%) | 95% CI | Range (months)
NSCLC | 21 | 13 (62) | 38, 82 | 3.7+, 31.3+
Thyroid Cancer | 5 | 5 (100) | 48, 100 | 4.7, 43.9+
Salivary Gland Cancer | 3 | 3 (100.0) | 29, 100 | 17.7+, 31.4+
Secretory carcinoma | 1 | PR | NA | 23.0+
Sarcoma, Soft tissue | 3 | 1 (33) | 0.8, 91 | 14.7+
Breast Cancer (adenocarcinoma) | 2 | PD, PD | NA | NA
Other* | 2 | SD, SD | NA | NA
Glioblastoma | 1 | SD | NA | NA
Cholangiocarcinoma | 1 | PD | NA | NA
Colorectal cancer | 1 | SD | NA | NA
Peripheral Nerve Sheath Tumor | 1 | PR | NA | 23.0+
* Includes esophageal cancer and head and neck cancer
PD: progressive disease; PR: partial response; SD: stable disease; NA: not applicable
“+” indicates ongoing response

Table 8: Efficacy Results by Tumor Type in TKI-pretreated NTRK Gene Fusion-Positive Patients
Tumor type | Patients (n=48) | ORR |  | DOR
Tumor type | Patients (n=48) | n (%) | 95% CI | Range (months)
NSCLC | 14 | 6 (43) | 18, 71 | 1.9, 23.0+
Salivary Gland Cancer | 8 | 7 (88) | 47, 100 | 3.7, 26.5+
Secretory carcinoma | 3 | 3 (100) | 29, 100 | 7.9, 26.5+
Sarcoma, Soft tissue | 6 | 1 (17) | 0.4, 64 | 5.6
Thyroid Cancer | 4 | 2 (50) | 7, 93 | 2.0, 9.6
Glioblastoma | 3 | 1 (33.3) | 0.8, 91 | 23.5
Cholangiocarcinoma | 2 | PR, PD | NA | 1.8
Colorectal cancer | 2 | PR, SD | NA | 17.5
Peripheral Nerve Sheath Tumor | 2 | PR, PR | NA | 5.5, 11.1
Neuroendocrine Tumor | 2 | PR, PR | NA | 5.5, 9.1
Pancreatic Cancer | 2 | PD, PD | NA | NA
Other* | 2 | SD, PD | NA | NA
Breast Cancer (adenocarcinoma) | 1 | PR | NA | 15.6+
* Includes gallbladder cancer and unknown primary cancer
PD: progressive disease; PR: partial response; SD: stable disease; NA: not applicable
“+” indicates ongoing response

ORR and DOR in adult patients are presented by NTRK gene fusion partner Tables 9 and 10 below.

Table 9: Efficacy Results by NTRK Gene Fusion Partner in TRK TKI-Naïve Patients
NTRK Partner | Subjects (n=40) | ORR |  | DOR
NTRK Partner | Subjects (n=40) | n (%) | 95% CI | Range (Months)
ETV6-NTRK3 | 12 | 9 (75) | (43, 95) | 4.7, 31.4+
TPM3-NTRK1 | 7 | 5 (71) | (29, 96) | 3.8, 23.1+
EML4-NTRK3 | 2 | Missing, PR | NA | 14.8+
IRF2BP2-NTRK1 | 2 | PR, PR | NA | 3.7+, 20.3+
PEAR1-NTRK1 | 2 | Missing, PD | NA | NA
Unknown | 2 | PD, SD | NA | NA
ATP2B2-IT2-NTRK1 | 1 | SD | NA | NA
GOLGB1-NTRK1 | 1 | SD | NA | NA
IL1RL2-NTRK2 | 1 | SD | NA | NA
LRPPRC-NTRK3 | 1 | SD | NA | NA
LRRC71-NTRK1 | 1 | Missing | NA | NA
Multiple | 1 | PR | NA | 28.6+
RBPMS-NTRK3 | 1 | PR | NA | 34.3+
SLC28A3-NTRK2 | 1 | PD | NA | NA
SQSTM1-NTRK1 | 1 | PR | NA | 15.7+
STRN3-NTRK1 | 1 | PR | NA | 23.9+
TMED3-NTRK3 | 1 | PD | NA | NA
TPR-NTRK1 | 1 | PR | NA | 43.9+
TRIM33-NTRK1 | 1 | CR | NA | 17.8+
PD: progressive disease; PR: partial response; SD: stable disease; NA: not applicable
“+” indicates ongoing response

Table 10: Efficacy Results by NTRK Gene Fusion Partner in TRK TKI-Pretreated Subjects
NTRK Partner | Subjects (n=48) | ORR |  | DOR
NTRK Partner | Subjects (n=48) | n (%) | 95% CI | Range (Months)
ETV6-NTRK3 | 24 | 16 (67) | (45, 84) | 1.8, 26.5+
EML4-NTRK3 | 5 | 4 (80) | (28, 99) | 1.9, 12.9
LMNA-NTRK1 | 4 | 1 (25) | (0.6, 81) | 5.6
TPM3-NTRK1 | 3 | 0 (0) | (0, 71) | NA
ATP1B1-NTRK1 | 1 | PD | NA | NA
BCR-NTRK2 | 1 | SD | NA | NA
ETV6-NTRK2 | 1 | NE | NA | NA
GP2-NTRK1 | 1 | PD | NA | NA
IRF2BP2-NTRK1 | 1 | Missing | NA | NA
KANK2-NTRK2 | 1 | PR | NA | 23.5
Multiple | 1 | PD | NA | NA
PRDX1-NTRK1 | 1 | Missing | NA | NA
RBPMS-NTRK3 | 1 | PD | NA | NA
SEL1L-NTRK1 | 1 | PD | NA | NA
SQSTM1-NTRK3 | 1 | PR | NA | 5.5
STRN3-NTRK3 | 1 | PR | NA | 11.1
PR = partial response; PD = progressive disease; SD = stable disease; NA = not applicable; NE = not evaluable
“+” indicates ongoing response

16 HOW SUPPLIED/STORAGE AND HANDLING

AUGTYRO (repotrectinib) 40 mg, Size 0, white opaque cap, white opaque body, hard shell capsules, filled with a white to off-white powder which may appear as a plug, imprinted with “REP 40” in blue text on the cap are supplied as follows:

- Bottles of 60 capsules (NDC 0003-4040-60)
- Bottles of 120 capsules (NDC 0003-4040-12)

AUGTYRO (repotrectinib) 160 mg, Size 0, blue opaque cap, blue opaque body, hard shell capsules, filled with a white to off-white powder which may appear as a plug, imprinted with “REP 160” in white text on the cap are supplied as follows:

- Bottles of 14 capsules (NDC 0003-4160-14)
- Bottles of 60 capsules (NDC 0003-4160-60)

Store at 20°C to 25°C (68°F to 77°F); excursions permitted between 15°C to 30°C (59°F to 86°F) [See USP Controlled Room Temperature].

17 PATIENT COUNSELING INFORMATION

Advise patients to read the FDA-approved patient labeling (Patient Information).

Central Nervous System (CNS) Effects

- Advise patients to inform their healthcare provider if they experience new or worsening CNS symptoms. Instruct patients not to drive or operate hazardous machinery if they are experiencing CNS adverse reactions [see Warnings and Precautions (5.1)].

Interstitial Lung Disease (ILD)/Pneumonitis

- Advise patients to inform their healthcare provider if they experience new or worsening pulmonary symptoms indicative of ILD/pneumonitis [see Warnings and Precautions (5.2)].

Hepatotoxicity

- Advise patients of the need for laboratory tests to monitor liver function and to immediately report symptoms of hepatotoxicity [see Warnings and Precautions (5.3)].

Myalgia with Creatine Phosphokinase Elevation

- Advise patients to inform their healthcare provider if they experience muscle pain [see Warnings and Precautions (5.4)].

Hyperuricemia

- Advise patients to inform their healthcare provider if they experience signs or symptoms associated with hyperuricemia [see Warnings and Precautions (5.5)].

Skeletal Fractures

- Inform patients that bone fractures have occurred in patients taking AUGTYRO and advise patients to report symptoms to their healthcare provider [see Warnings and Precautions (5.6)].

Embryo-Fetal Toxicity

- Advise pregnant women and females of reproductive potential of the potential risk to a fetus. Advise females to inform their healthcare provider of a known or suspected pregnancy [see Warnings and Precautions (5.7), Use in Specific Populations (8.1, 8.3)].
- Advise females of reproductive potential to use effective non-hormonal contraception during treatment with AUGTYRO and for 2 months after the last dose, since AUGTYRO can render some hormonal contraceptives ineffective [see Drug Interactions (7.2)].
- Advise male patients with female partners of reproductive potential to use effective contraception during treatment with AUGTYRO and for 4 months after the last dose [see Use in Specific Populations (8.1, 8.3)].

Lactation

- Advise females not to breastfeed during treatment with AUGTYRO and for 10 days after the last dose [see Use in Specific Populations (8.2)].

Drug Interactions

- Advise patients to inform their healthcare providers of all concomitant medications, including prescription medicines, over-the-counter drugs, vitamins, and herbal products [see Drug Interactions (7)].
- Advise patients to avoid grapefruit or grapefruit juice while taking AUGTYRO [see Drug Interactions (7)].
- Advise patients that hormonal contraceptives can be ineffective while taking AUGTYRO [see Drug Interactions (7)].

Administration

- Advise patients to swallow AUGTYRO capsules whole with or without food [see Dosage and Administration (2.6), Pharmacokinetics (12.3)].
- Instruct patients if they miss a dose, or vomit at any time after taking a dose of AUGTYRO, not to “make it up,” but take the next dose of AUGTYRO at the next scheduled time [see Dosage and Administration (2.6)].

For more information, go to www.AUGTYRO.com or call 1-877-284-8976.

Distributed by:
Bristol-Myers Squibb Company
Princeton, NJ 08543 USA
U.S. License No. 1713

AUGTYROTM is a trademark of Turning Point Therapeutics, Inc., a Bristol Myers Squibb company.

Patient Package Insert

PATIENT INFORMATION
AUGTYRO™ [Aug-TYE-ro]

(repotrectinib)

capsules

What is the most important information I should know about AUGTYRO?

AUGTYRO may cause serious side effects, including:

- Central nervous system (CNS) effects. Tell your healthcare provider right away if you experience any new or worsening symptoms of CNS effects during treatment with AUGTYRO, including:

  - dizziness
  - vertigo
  - changes in mood, such as anxiety, irritability, and depression
  - balance or coordination problems

- problems with thinking, such as forgetfulness or confusion
- seeing or hearing things that are not real (hallucinations)
- problems with concentration, attention, memory, and sleep

- Lung problems (pneumonitis). Tell your healthcare provider if you have any new or worsening symptoms of lung problems, including a dry cough (without mucus), productive cough (with mucus), wheezing, or trouble breathing.
- Liver problems. Your healthcare provider will do blood tests to check your liver function before starting treatment with AUGTYRO, every 2 weeks for the first month and as needed during treatment. Tell your healthcare provider right away if you develop symptoms of liver problems including:

  - your skin or the white part of your eyes turns yellow
  - dark or “tea-colored” urine
  - light-colored stools (bowel movements)

- loss of appetite
- nausea or vomiting
- pain on the upper right side of your stomach area

- Muscle problems. Your healthcare provider will do blood tests before starting treatment with AUGTYRO, every 2 weeks for the first month and as needed during treatment. Tell your healthcare provider right away if you get new or worsening signs and symptoms of muscle problems, including unexplained muscle pain or muscle pain that does not go away, tenderness, or weakness.
- Increased uric acid level in your blood (hyperuricemia). AUGTYRO may cause an excess of uric acid in your blood. Your healthcare provider will do tests before and during your treatment with AUGTYRO to check the uric acid level in your blood. Your healthcare provider may prescribe medicines if you have high blood uric acid levels. Tell your healthcare provider if you experience symptoms of increased uric acid including:

  - red, hot, tender, or swollen joints, especially in your big toe
  - pain in your stomach-area or sides
  - decrease in your amount of urine or no urine at all

- nausea or vomiting
- pink or brown urine or blood in your urine

- Bone fractures. AUGTYRO may increase your risk for bone fractures. Bone fractures may happen with or without a fall or other injury. Tell your healthcare provider right way if you have pain, changes in movement, or bone abnormalities.

See “What are the possible side effects of AUGTYRO?” for more information about side effects.

What is AUGTYRO?

AUGTYRO is a prescription medicine used to treat:

- adults with non-small cell lung cancer (NSCLC) that has spread within your chest or to other parts of the body and is caused by an abnormal ROS1 gene.
- adults and children 12 years of age and older with solid tumors (cancer) that:
- are caused by certain abnormal NTRK genes, and
- have spread to other parts of the body, or if surgery to remove your cancer is likely to cause severe complications, and
- have grown or spread after other treatment or there is no satisfactory alternative treatment option.

It is not known if AUGTYRO is safe and effective in children with ROS1-positive NSCLC or in children younger than 12 years of age with NTRK-positive solid tumors.

Before taking AUGTYRO, tell your healthcare provider about all your medical conditions, including if you:

- have nervous system (neurological) problems.
- have lung or breathing problems other than lung cancer.
- have liver or kidney problems.
- are pregnant or plan to become pregnant. AUGTYRO can harm your unborn baby. Tell your healthcare provider right away if you become pregnant or think you may be pregnant during treatment with AUGTYRO.

Females who are able to become pregnant:

- Your healthcare provider should do a pregnancy test before you start treatment with AUGTYRO.
- You should use effective non-hormonal birth control (contraception) during treatment and for 2 months after the last dose of AUGTYRO.
- Birth control methods that contain hormones (such as birth control pills, injections, or transdermal system patches) may not work as well during treatment with AUGTYRO.
- Talk to your healthcare provider about birth control methods that may be right for you.

Males with female partners who are able to become pregnant:

- You should use effective birth control during treatment with AUGTYRO and for 4 months after the last dose.

- are breastfeeding or plan to breastfeed. It is not known if AUGTYRO passes into your breast milk. Do not breastfeed during treatment and for 10 days after the last dose of AUGTYRO. Talk to your healthcare provider about the best way to feed your baby during this time.

Tell your healthcare provider about all the medicines you take, including prescription and over-the-counter medicines, vitamins, or herbal supplements.

Taking AUGTYRO with certain other medicines may affect the amount of AUGTYRO or other medicines in your blood and may cause side effects or affect the way that AUGTYRO or other medicines work. Know the medicines you take. Keep a list of them to show your healthcare provider and pharmacist when you get a new medicine.

How should I take AUGTYRO?

- Take AUGTYRO exactly as your healthcare provider tells you to take it. Do not change your dose or stop taking AUGTYRO unless your healthcare provider tells you to.
- Your healthcare provider may change your dose, temporarily stop, or permanently stop treatment with AUGTYRO if you develop side effects.
- Take AUGTYRO at about the same time each day with or without food.
- Swallow AUGTYRO capsules whole with water. Do not open, crush, chew or dissolve the capsule. Do not take a capsule if it is broken, cracked, or damaged.
- If you miss a dose, or vomit at any time after taking a dose of AUGTYRO, do not take an extra dose. Just skip the dose and take your next dose at the regularly scheduled time. Do not take 2 doses at the same time to make up a missed or vomited dose.

What should I avoid while taking AUGTYRO?

- You should not drink grapefruit juice or eat grapefruit during your treatment with AUGTYRO. It may increase the amount of AUGTYRO in your blood to a harmful level.
- Do not drive or operate machinery until you know how AUGTYRO affects you. If you experience dizziness, blurred vision, memory loss, changes in mental status, confusion, hallucinations or have trouble with balance or coordination or problems with concentration and attention, do not drive or operate machinery until your symptoms have resolved.

What are the possible side effects of AUGTYRO?

AUGTYRO may cause serious side effects, including:

- See “What is the most important information I should know about AUGTYRO?”

The most common side effects of AUGTYRO include:

- dizziness
- change in sense of taste
- feeling of numbness or tingling in your arms or legs
- constipation
- shortness of breath

- tiredness
- trouble with balance, coordination, and walking
- problems with thinking, such as forgetfulness or confusion, memory problems and hallucinations
- muscle weakness
- nausea

These are not all of the possible side effects of AUGTYRO.

Call your doctor for medical advice about side effects. You may report side effects to FDA at 1-800-FDA-1088.

How should I store AUGTYRO?

- Store AUGTYRO at room temperature between 68°F to 77°F (20°C to 25°C).

Keep AUGTYRO and all medicines out of the reach of children.

General information about the safe and effective use of AUGTYRO.

Medicines are sometimes prescribed for purposes other than those listed in a Patient Information leaflet. Do not use AUGTYRO for a condition for which it was not prescribed. Do not give AUGTYRO to other people, even if they have the same symptoms that you have. It may harm them. You can ask your pharmacist or healthcare provider for information about AUGTYRO that is written for health professionals.

What are the ingredients of AUGTYRO?

Active ingredient: repotrectinib

Inactive ingredients: microcrystalline cellulose, sodium lauryl sulfate, croscarmellose sodium, and colloidal silicon dioxide. Capsule shell contains gelatin and titanium dioxide. Printing ink contains shellac.

- White opaque capsules, printing ink contains in addition FD & C blue #2 aluminum lake.
- Blue opaque capsules contain in addition magnesium stearate and FD & C blue #1. Printing ink contains in addition titanium dioxide.

Distributed by: Bristol-Myers Squibb Company, Princeton, NJ 08543 USA; U.S. License No. 1713

AUGTYROTM is a trademark of Turning Point Therapeutics, Inc., a Bristol Myers Squibb company.

For more information, go to www.AUGTYRO.com or call 1-877-284-8976.

This Patient Information has been approved by the U.S. Food and Drug Administration. Revised: 06/2024

PACKAGE/LABEL PRINCIPAL DISPLAY PANEL

NDC 0003-4160-14
14 Capsules

AUGTYROTM
(repotrectinib)
capsules
160mg
Swallow capsules whole
Rx only
Bristol Myers Squibb

NDC 0003-4160-14
14 Capsules

AUGTYROTM
(repotrectinib)
capsules
160mg
Swallow capsules whole
Rx only
Bristol Myers Squibb

NDC 0003-4040-60
60 Capsules

AUGTYROTM
(repotrectinib)
capsules
40mg
Swallow capsules whole
Rx only
Bristol Myers Squibb

NDC 0003-4040-60
60 Capsules

AUGTYROTM
(repotrectinib)
capsules
40mg
Swallow capsules whole
Rx only
Bristol Myers Squibb

NDC 0003-4040-12
120 Capsules

AUGTYROTM
(repotrectinib)
capsules
40mg
Swallow capsules whole
Rx only
Bristol Myers Squibb